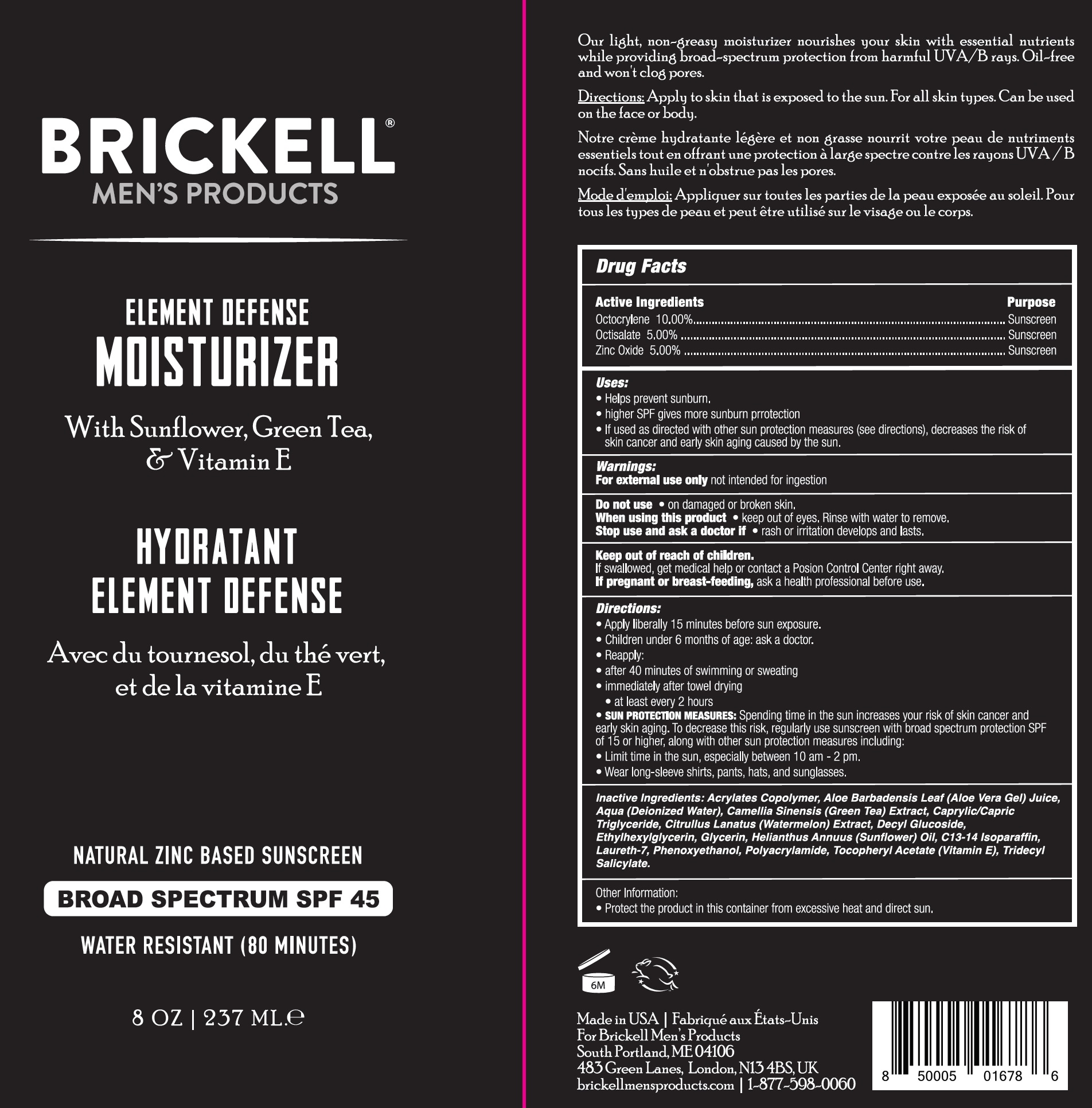 DRUG LABEL: BRICKELL Element Defense Moisturizer SPF-45
NDC: 82247-234 | Form: CREAM
Manufacturer: BRICKELL BRANDS LLC
Category: otc | Type: HUMAN OTC DRUG LABEL
Date: 20231111

ACTIVE INGREDIENTS: OCTOCRYLENE 100 mg/1 mL; OCTISALATE 50 mg/1 mL; ZINC OXIDE 50 mg/1 mL
INACTIVE INGREDIENTS: ALOE VERA LEAF; WATER; GREEN TEA LEAF; MEDIUM-CHAIN TRIGLYCERIDES; WATERMELON; DECYL GLUCOSIDE; ETHYLHEXYLGLYCERIN; GLYCERIN; SUNFLOWER OIL; C13-14 ISOPARAFFIN; LAURETH-7; PHENOXYETHANOL; .ALPHA.-TOCOPHEROL ACETATE; TRIDECYL SALICYLATE

BRICKELL Element Defense Moisturizer SPF-45

Active Ingredients

Octocrylene 10.00% Octisalate 5.00% Zinc Oxide 5.00%

Purpose

Sunscreen

Uses:

- Helps prevent sunburn.
- higher SPF gives more sunburn protection
- If used as directed with other sun protection measures (see directions), decreases the risk of skin cancer and early skin aging caused by the sun.

Warnings:

not intended for ingestion For external use only

Do not use

- on damaged or broken skin.

When using this product

- keep out of eyes. Rinse with water to remove.

Stop use and ask a doctor if

- rash or irritation develops and lasts.

Keep out of reach of children.

If swallowed, get medical help or contact a Poison Control Center right away.

If pregnant or breast-feeding,

ask a health professional before use.

Directions:

- Apply liberally 15 minutes before sun exposure.
- Children under 6 months of age: ask a doctor.
- Reapply:
- after 40 minutes of swimming or sweating
- immediately after towel drying
- at least every2 hourr
- Spending time in the sun increases your risk of skin cancer and early skin aging. To decrease this risk, regularly use sunscreen with broad spectrum protection SPF of 15 or higher, along with other sun protection measues including: SUN PROTECTION MEASURES:
- Limit time in the sun, especially between 10 am - 2 pm.
- Wear long-sleeve shirts, pants, hats and sunglasses.

Inactive Ingredients:

Acrylates Copolymer, Aloe Barbadensis Leaf (Aloe Vera Gel) Juice, Aqua (Deionized Water), Camellia Sinensis (Green Tea) Extract, Caprylic/Capric Triglyceride, Citrullus Lantatus (Watermelon) Extract, Decyl Glucoside, Ethylhexylglycerin, Glycerin, Helianthus Annuus (Sunflower) Oil, C13-14 Isoparaffin, Laureth-7, Phenoxyethanol, polyacrylamide, Tocopheryl Acetate (Vitamin E), Tridecyl Salicylate.

Other Information:

- Protect the product in this container from excessive heat and direct sun.